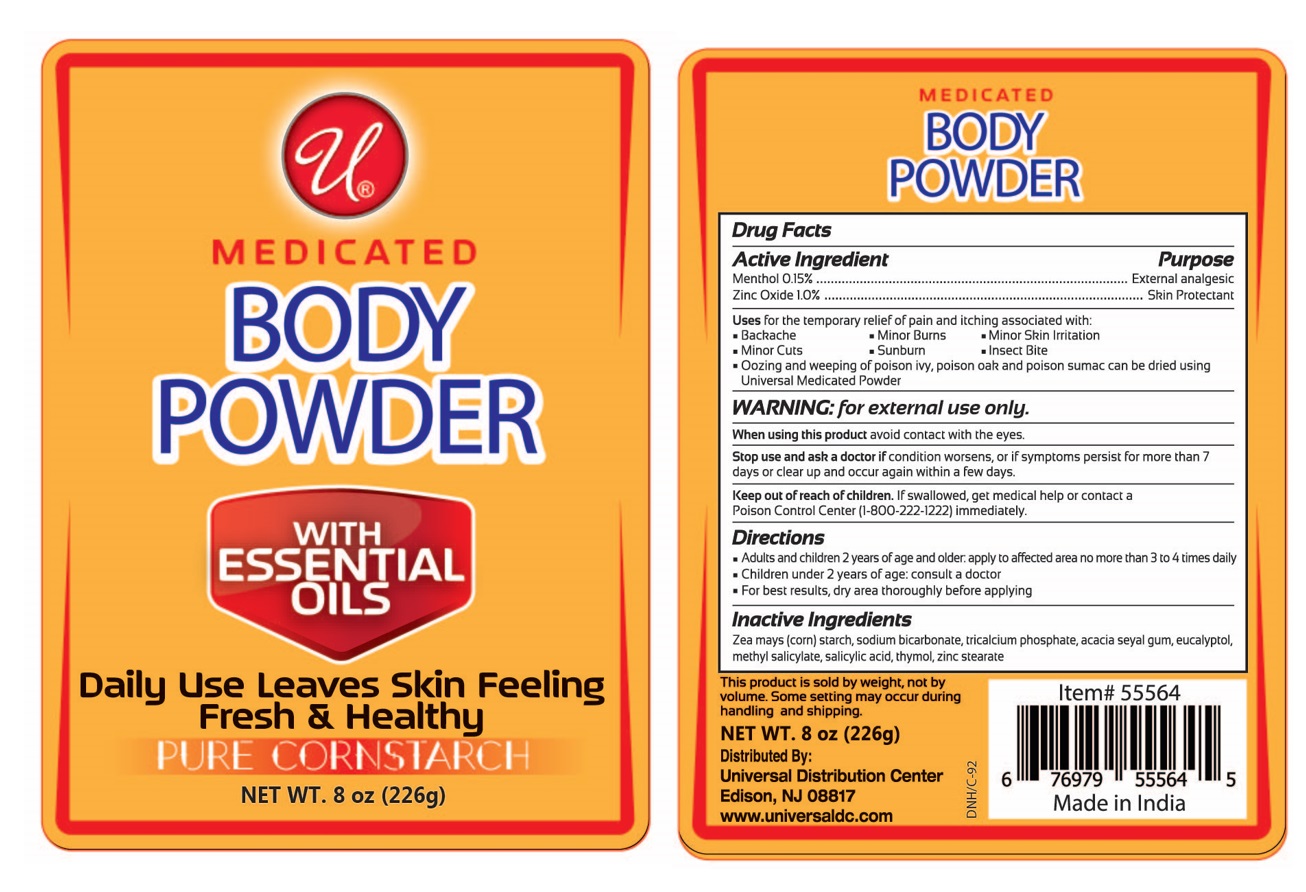 DRUG LABEL: Medicated Body
NDC: 52000-038 | Form: POWDER
Manufacturer: Universal Distribution Center LLC
Category: otc | Type: HUMAN OTC DRUG LABEL
Date: 20240619

ACTIVE INGREDIENTS: MENTHOL, UNSPECIFIED FORM 1.5 mg/1 g; ZINC OXIDE 10 mg/1 g
INACTIVE INGREDIENTS: STARCH, CORN; SODIUM BICARBONATE; TRICALCIUM PHOSPHATE; GUM TALHA; EUCALYPTOL; METHYL SALICYLATE; SALICYLIC ACID; THYMOL; ZINC STEARATE

Medicated Body Powder

Active Ingredient

Menthol 0.15%

Zinc Oxide 1.0%

Purpose

External analgesic

Skin Protectant

Uses

for the temporary relief of pain and itching associated with

• Backache • Minor Burn • Minor Skin Irritations

• Minor Cut • Sunburn • Insect Bites

• Ooozing and weeping of poison ivy, poison oak and poison sumac can be dried using Universal Medicated Powder

WARNING

for external use only.

When using this product avoid contact with the eyes.

Stop use and ask a doctor if condition worsens, or if symptoms persist for more than 7 days or clear up and occur again within a few days.

Keep out of reach of children. If swallowed, get medical help or contact a Poison Control Center (1-800-222-1222) immediately.

Directions

- Adults and children 2 years of age and older: apply to affected area no more than 3 to 4 times daily
- Children under 2 years of age: consult a doctor
- For best results, dry area thoroughly before applying

Inactive Ingredients

Zea mays (corn) starch, sodium bicarbonate, tricalcium phosphate, acacia seyal gum, eucalyptol, methyl salicylate, salicylic acid, thymol, zinc stearate

WITH ESSENTIAL OILS

Daily Use Leaves Skin Feeling Fresh & Healthy

PURE CORNSTARCH

This product is sold by weight, not by volume. Some settling may occur during handling and shipping.

Distributed By:
Universal Distribution Center
Edison, NJ 08817
www.universaldc.com

Made in India